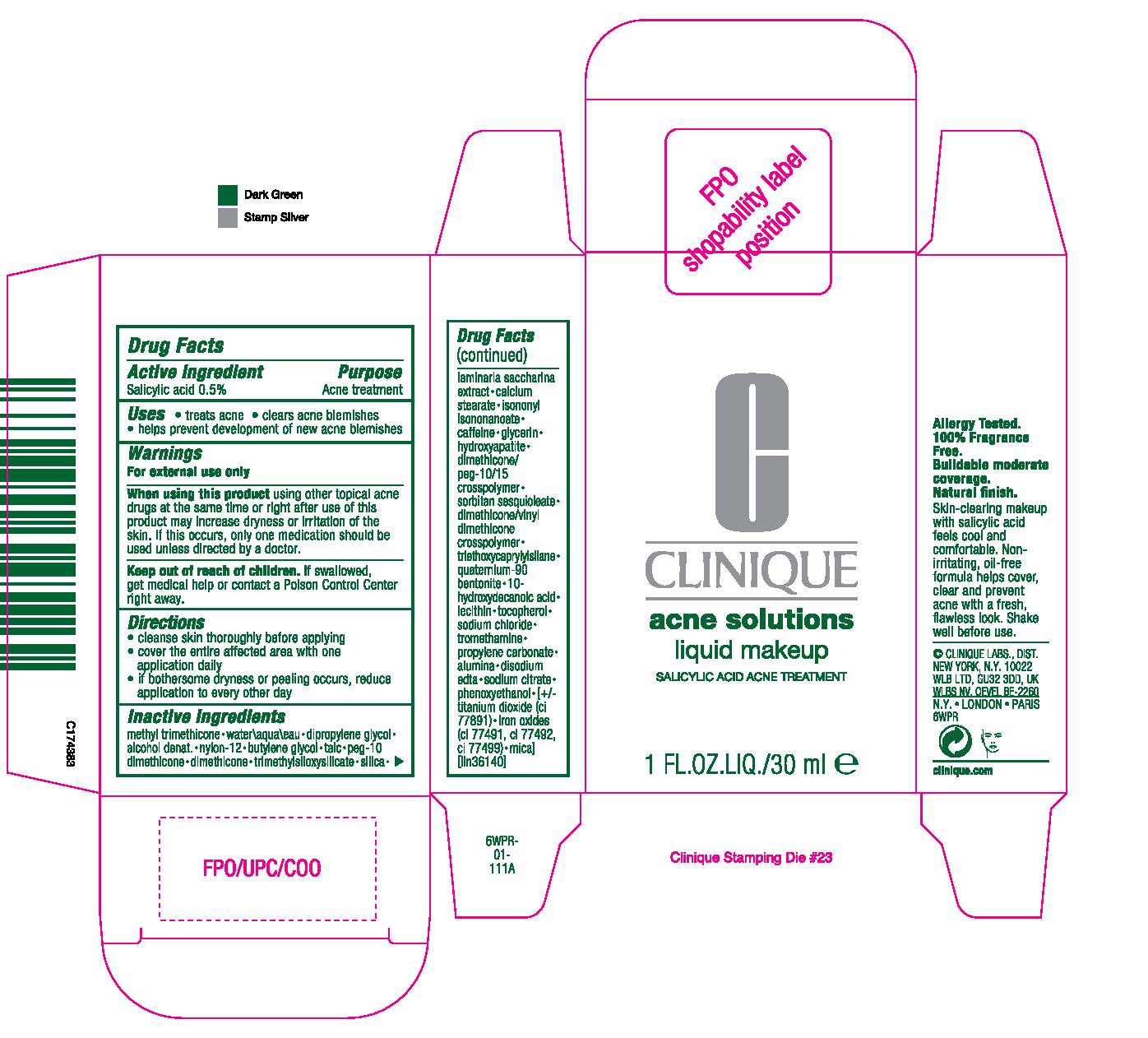 DRUG LABEL: ACNE solutions liquid MAKEUP
NDC: 49527-751 | Form: LIQUID
Manufacturer: CLINIQUE LABORATORIES LLC
Category: otc | Type: HUMAN OTC DRUG LABEL
Date: 20241225

ACTIVE INGREDIENTS: SALICYLIC ACID 5 mg/1 mL
INACTIVE INGREDIENTS: PROPYLENE CARBONATE; ALUMINUM OXIDE; DISODIUM EDTA-COPPER; SODIUM CITRATE, UNSPECIFIED FORM; PHENOXYETHANOL; TITANIUM DIOXIDE; FERRIC OXIDE RED; FERRIC OXIDE YELLOW; FERROSOFERRIC OXIDE; MICA; METHYL TRIMETHICONE; WATER; DIPROPYLENE GLYCOL; ALCOHOL; NYLON-12; BUTYLENE GLYCOL; TALC; BIS-PEG-10 DIMETHICONE/DIMER DILINOLEATE COPOLYMER; DIMETHICONE; TRIMETHYLSILOXYSILICATE (M/Q 0.6-0.8); SILICA DIMETHYL SILYLATE; SACCHARINA LATISSIMA; CALCIUM STEARATE; ISONONYL ISONONANOATE; CAFFEINE; GLYCERIN; TRIBASIC CALCIUM PHOSPHATE; DIMETHICONE CROSSPOLYMER (450000 MPA.S AT 12% IN CYCLOPENTASILOXANE); SORBITAN SESQUIOLEATE; DIMETHICONE/VINYL DIMETHICONE CROSSPOLYMER (HARD PARTICLE); TRIETHOXYCAPRYLYLSILANE; BENTONITE; 10-HYDROXYDECANOIC ACID; LECITHIN, SOYBEAN; TOCOPHEROL; SODIUM CHLORIDE; TROMETHAMINE

ACNE solutions liquid MAKEUP

ACTIVE INGREDIENT: SALICYLIC ACID 0.5%

PURPOSE: ACNE TREATMENT

USES:

- TREATS ACNE
- HELPS PREVENT DEVELOPMENT OF NEW ACNE BLEMISHES

WARNINGS: FOR EXTERNAL USE ONLY.

WHEN USING THIS PRODUCT: USING OTHER TOPICAL ACNE DRUGS AT THE SAME TIME OR RIGHT AFTER USE OF THIS PRODUCT MAY INCREASE DRYNESS OR IRRITATION OF THE SKIN. IF THIS OCCURS, ONLY ONE MEDICATION SHOULD BE USED UNLESS DIRECTED BY A DOCTOR.

KEEP OUT OF REACH OF CHILDREN. IF SWALLOWED, GET MEDICAL HELP OR CONTACT A POISON CONTROL CENTER RIGHT AWAY.

DIRECTIONS

- SHAKE WELL BEFORE USE
- CLEANSE SKIN THOROUGHLY BEFORE APPLYING
- COVER THE ENTIRE AFFECTED AREA WITH ONE APPLICATION
- GRADUALLY INCREASE TO 2 OR 3 TIMES DAILY IF NEEDED OR AS DIRECTED BY A DOCTOR
- IF BOTHERSOME DRYNESS OR PEELING OCCURS, REDUCE APPLICATION TO EVERY OTHER DAY.

INACTIVE INGREDIENTS:

METHYL TRIMETHICONE [] WATER [] DIPROPYLENE GLYCOL [] ALCOHOL DENAT. [] NYLON-12 [] BUTYLENE GLYCOL [] TALC [] PEG-10 DIMETHICONE [] DIMETHICONE [] TRIMETHYLSILOXYSILICATE [] SILICA [] LAMINARIA SACCHARINA EXTRACT [] CALCIUM STEARATE [] ISONONYL ISONONANOATE [] CAFFEINE [] GLYCERIN [] HYDROXYAPATITE [] DIMETHICONE/PEG-10/15 CROSSPOLYMER [] SORBITAN SESQUIOLEATE [] DIMETHICONE/VINYL DIMETHICONE CROSSPOLYMER [] TRIETHOXYCAPRYLYLSILANE [] QUATERNIUM-90 BENTONITE [] 10-HYDROXYDECANOIC ACID [] LECITHIN [] TOCOPHEROL [] SODIUM CHLORIDE [] TROMETHAMINE [] PROPYLENE CARBONATE [] ALUMINA [] DISODIUM EDTA [] SODIUM CITRATE [] PHENOXYETHANOL MAY CONTAIN: TITANIUM DIOXIDE [] IRON OXIDES[] MICA ILN36140

PACKAGE LABEL

PRINCIPLE DISPLAY PANEL 1 FL OZ/ 30 ML FOLDING CARTON
CLINIQUE ACNE SOLUTIONS
LIQUID MAKEUP
SALICYLIC ACID ACNE TREATMENT
1 FL OZ / 30 mL
CLINIQUE LABS DISTR
NY, NY 10022
6WPR
CLINIQUE.COM